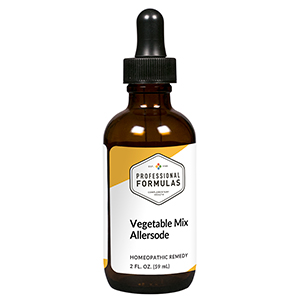 DRUG LABEL: Vegetable Mix
NDC: 63083-1018 | Form: LIQUID
Manufacturer: Professional Complementary Health Formulas
Category: homeopathic | Type: HUMAN OTC DRUG LABEL
Date: 20190815

ACTIVE INGREDIENTS: SUS SCROFA ADRENAL GLAND 6 [hp_X]/59 mL; CORTICOTROPIN 6 [hp_X]/59 mL; HISTAMINE DIHYDROCHLORIDE 12 [hp_X]/59 mL; BEEF LIVER 6 [hp_X]/59 mL; ASPARAGUS 6 [hp_X]/59 mL; LIMA BEAN 6 [hp_X]/59 mL; BEET 6 [hp_X]/59 mL; BROCCOLI 6 [hp_X]/59 mL; CABBAGE 6 [hp_X]/59 mL; CARROT 6 [hp_X]/59 mL; CAULIFLOWER 6 [hp_X]/59 mL; CELERY 6 [hp_X]/59 mL; CORN 6 [hp_X]/59 mL; CUCUMBER 6 [hp_X]/59 mL; GARLIC 6 [hp_X]/59 mL; KALE 6 [hp_X]/59 mL; LENTIL 6 [hp_X]/59 mL; LETTUCE 6 [hp_X]/59 mL; ONION 6 [hp_X]/59 mL; PARSNIP 6 [hp_X]/59 mL; CHICKPEA 6 [hp_X]/59 mL; PEPPERS 6 [hp_X]/59 mL; POTATO 6 [hp_X]/59 mL; RADISH 6 [hp_X]/59 mL; SOYBEAN 6 [hp_X]/59 mL; SPINACH 6 [hp_X]/59 mL; TURNIP 6 [hp_X]/59 mL
INACTIVE INGREDIENTS: ALCOHOL; WATER

AVEG

ACTIVE INGREDIENTS

Adrenal 6X
ACTH 6X, 30X
Histaminum hydrochloricum 12X
Liver 6X, 12X
and all the following at 6X, 12X, 60X, 100X:
Asparagus
Bean (lima/navy/string)
Beet
Broccoli
Cabbage
Carrot
Cauliflower
Celery
Corn
Cucumber
Garlic
Kale
Lentil
Lettuce
Onion
Parsnip
Pea (chick/green)
Peppers (green/red)
Potato (red/white)
Radish
Soybean
Spinach
Turnip

QUESTIONS

Professional Formulas

PO Box 2034 Lake Oswego, OR 97035

INDICATIONS

For the temporary relief of gas, bloating, diarrhea, and itching of the nose or throat due to sensitivity to vegetables and legumes.*

PURPOSE

*Claims based on traditional homeopathic practice, not accepted medical evidence. Not FDA evaluated.

WARNINGS

Severe symptoms such as difficulty breathing, facial swelling, dizziness, confusion, and hives may be life-threatening and require immediate emergency care. Keep out of the reach of children. In case of overdose, get medical help or contact a poison control center right away. If pregnant or breastfeeding, ask a healthcare professional before use.

Keep out of the reach of children.

PREGNANCY OR BREAST FEEDING

If pregnant or breastfeeding, ask a healthcare professional before use.

DIRECTIONS

Place drops under tongue 30 minutes before/after meals. Adults and children 12 years and over: Take 10 to 15 drops up to 3 times per day. For desensitization, begin with 1 to 5 drops daily, increasing to the standard dose gradually to avoid symptom expression; after 1 to 3 months at the standard dose, decrease gradually to a maintenance dose of 10 to 15 drops weekly. Consult a physician for use in children under 12 years of age.

OTHER INFORMATION

Tamper resistant. If seal is broken, do not use. After opening, close container tightly and store at room temperature away from heat.

INACTIVE INGREDIENTS

20% ethanol, purified water.

LABEL

Est 1985

Professional Formulas

Complementary Health

Vegetable Mix

Homeopathic Remedy

2 FL. OZ. (59 mL)